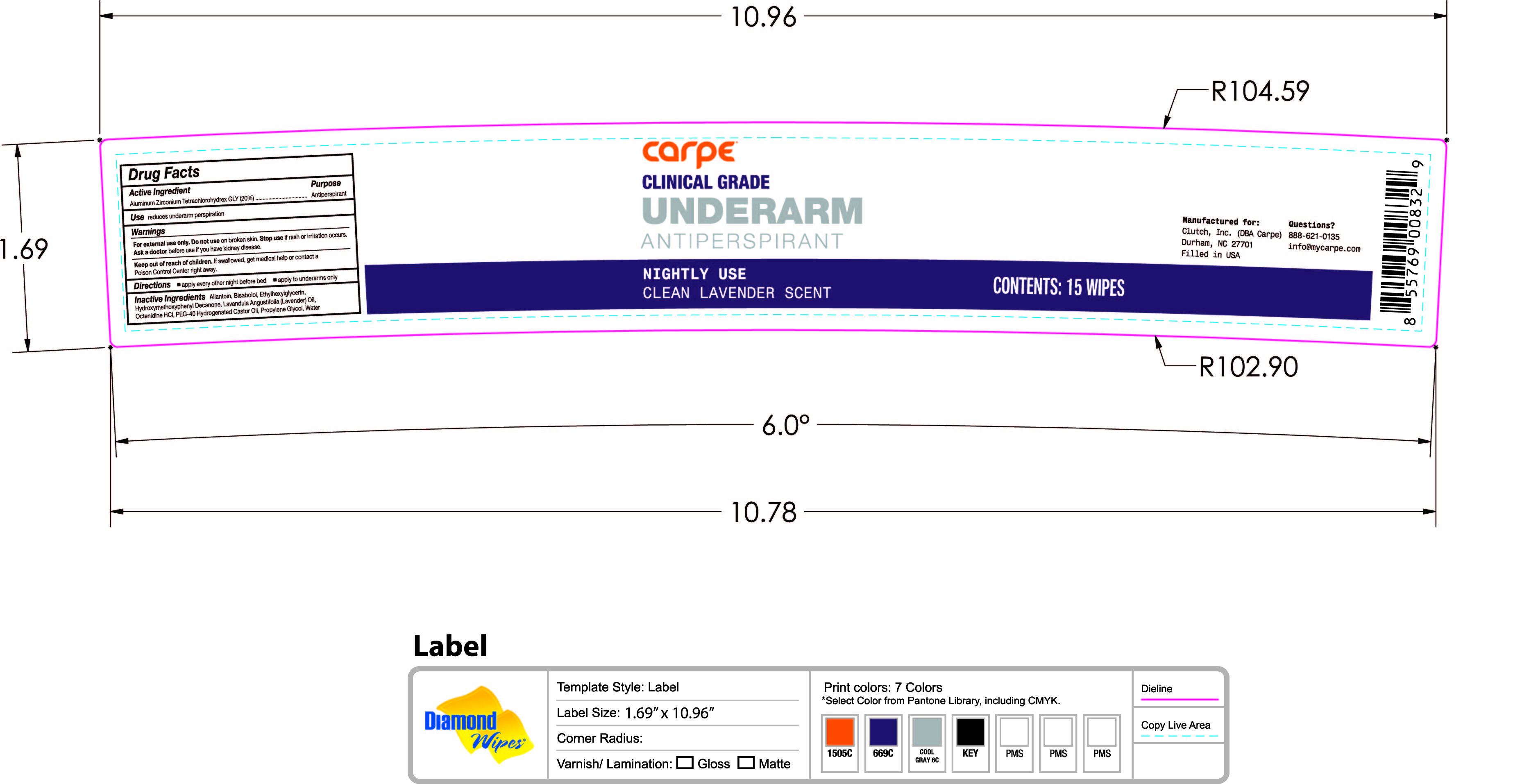 DRUG LABEL: Underarm Antiperspirant PM Wipes Clean Lavender Scent
NDC: 74307-010 | Form: SOLUTION
Manufacturer: Clutch Inc
Category: otc | Type: HUMAN OTC DRUG LABEL
Date: 20251211

ACTIVE INGREDIENTS: ALUMINUM ZIRCONIUM TETRACHLOROHYDREX GLY 20 g/100 g
INACTIVE INGREDIENTS: LAVENDER OIL; OCTENIDINE HYDROCHLORIDE; PROPYLENE GLYCOL; WATER; POLYOXYL 40 HYDROGENATED CASTOR OIL; ALLANTOIN; LEVOMENOL; ETHYLHEXYLGLYCERIN; 1-(4-HYDROXY-3-METHOXYPHENYL)-DECAN-3-ONE

Underarm Antiperspirant PM Wipes Clean Lavender Scent

Active Ingredients Purpose
Aluminum Zirconium Tetrachlorohydrex Gly 20% Antiperspirant

PURPOSE

Usereduce underarm perspiration

Keep out of reach of children.If swallowed, get medical help or contact a Poison Control Center

Stop use if rash or irritation occurs.

Warnings
For external use only. Do not useon broken skin.
Ask a doctorbefore use if you have kidney disease

Directions

- apply every other night before bed
- apply to underarm only

INACTIVE INGREDIENT

Inactive IngredientsAllantoin, Bisabolol, Ethylhexylglycerin, Hydroxymethoxyphenyl Decanone, Lavandula Angustifolia (Lavender) Oil, Octenidine HCL, PEG-40 Hydrogenated Castor Oil, Propylene Glycol, Water

PACKAGE LABEL

carpe

Clinical Grade

Underarm

Antiperspirant

Nightly Use

Clean Lavender Scent

Contents: 15 wipes